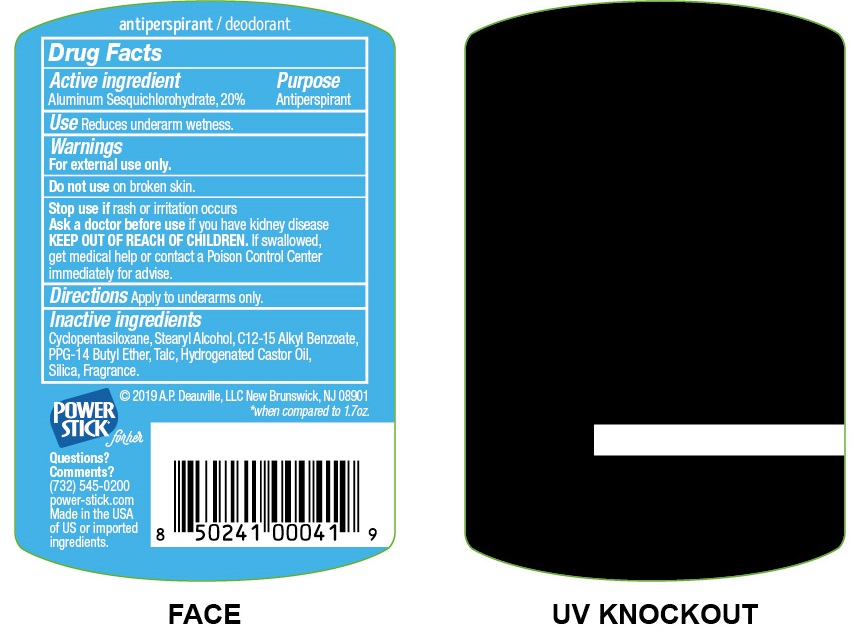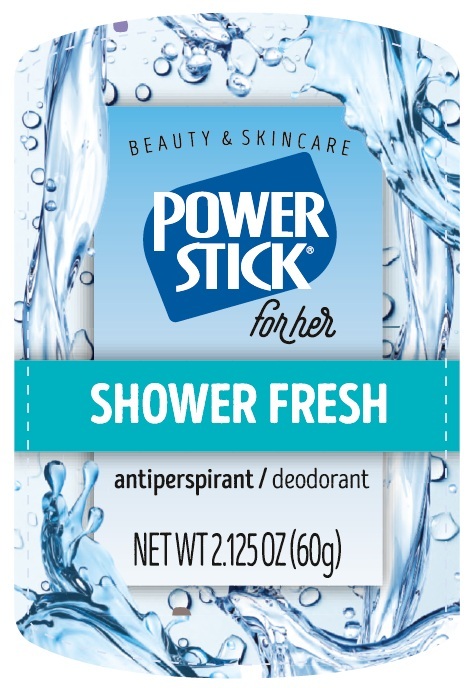 DRUG LABEL: Power Stick for Her Shower Fresh
NDC: 42913-026 | Form: STICK
Manufacturer: A.P. Deauville, LLC
Category: otc | Type: HUMAN OTC DRUG LABEL
Date: 20260224

ACTIVE INGREDIENTS: ALUMINUM SESQUICHLOROHYDRATE 200 mg/1 g
INACTIVE INGREDIENTS: CYCLOMETHICONE 5; STEARYL ALCOHOL; ALKYL (C12-15) BENZOATE; PPG-14 BUTYL ETHER; TALC; HYDROGENATED CASTOR OIL; SILICON DIOXIDE

Power Stick for Her Shower Fresh

Active ingredient

Aluminum Sesquichlorohydrate, 20%

Purpose

Antiperspirant

Use

Reduces underarm wetness.

Warnings

For external use only.

Do not use

on broken skin.

Stop use if

rash or irritation occurs

Ask a doctor before use

if you have kidney disease

KEEP OUT OF REACH OF CHILDREN.

If swallowed, get medical help or contact a Poison Control Center immediately for advise.

Directions

Apply to underarms only.

Inactive ingredients

Cyclopentasiloxane, Stearyl Alcohol, C12-15 Alkyl Benzoate, PPG-14 Butyl Ether, Talc, Hydrogenated Castor Oil, Silica, Fragrance.

Questions? Comments?

(732) 545-0200 power-stick.com